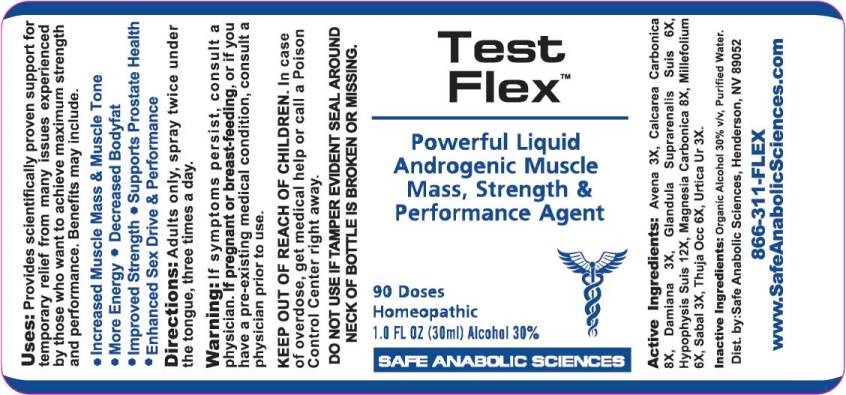 DRUG LABEL: Test Flex
NDC: 49215-0006 | Form: SPRAY
Manufacturer: Safe Anabolic Sciences
Category: homeopathic | Type: HUMAN OTC DRUG LABEL
Date: 20170817

ACTIVE INGREDIENTS: AVENA SATIVA FLOWERING TOP 3 [hp_X]/1 mL; OYSTER SHELL CALCIUM CARBONATE, CRUDE 8 [hp_X]/1 mL; TURNERA DIFFUSA LEAFY TWIG 3 [hp_X]/1 mL; SUS SCROFA ADRENAL GLAND 6 [hp_X]/1 mL; SUS SCROFA PITUITARY GLAND 12 [hp_X]/1 mL; MAGNESIUM CARBONATE 8 [hp_X]/1 mL; ACHILLEA MILLEFOLIUM 6 [hp_X]/1 mL; SAW PALMETTO 3 [hp_X]/1 mL; THUJA OCCIDENTALIS LEAF 6 [hp_X]/1 mL; URTICA URENS 3 [hp_X]/1 mL
INACTIVE INGREDIENTS: WATER; ALCOHOL

Drug Facts:

ACTIVE INGREDIENTS:

Avena Sativa 3X, Calcarea Carbonica 8X, Damiana 3X, Glandula Suprarenalis Suis 6X, Hypophysis Suis 12X, Magnesia Carbonica 8X, Millefolium 6X, Hypophysis Suis 12X, Sabal Serrulata 3X, Thuja Occidentalis 6X, Urtica Urens 3X.

USES:

Provides scientifically proven support for temporary relief from many issues experienced by those who want to achieve maximum strength and performance. Benefits may include:

• Increased Muscle Mass & Muscle Tone
• More Energy
• Decreased Bodyfat
• Improved Strength
• Supports Prostate Health
• Enhanced Sex Drive & Performance

WARNINGS:

If symptoms persist, consult a physician.

If pregnant or breast-feeding, or if you have a pre-existing medical condition, consult a physician prior to use.

KEEP OUT OF REACH OF CHILDREN. In case of overdose, get medical help or call a Poison Control Center right away.

DO NOT USE IF TAMPER EVIDENT SEAL AROUND NECK OF BOTTLE IS BROKEN OR MISSING.

KEEP OUT OF REACH OF CHILDREN. In case of overdose, get medical help or call a Poison Control Center right away.

DIRECTIONS:

Adults only, spray twice under the tongue, three times a day.

INDICATIONS:

Provides scientifically proven support for temporary relief from many issues experienced by those who want to achieve maximum strength and performance. Benefits may include:

• Increased Muscle Mass & Muscle Tone
• More Energy
• Decreased Bodyfat
• Improved Strength
• Supports Prostate Health
• Enhanced Sex Drive & Performance

INACTIVE INGREDIENTS:

Purified Water, Organic Ethanol 30%

QUESTIONS:

Dist. by: Safe Anabolic Sciences, Henderson, NV 89052

866-311-FLEX

www.SafeAnabolicSciences.com

PACKAGE DISPLAY LABEL:

Test

Flex

Powerful Liquid

Androgenic Muscle

Mass, Strength &

Performance Agent

90 Doses
Homeopathic
1.0 FL OZ (30ml) Alcohol 30%

SAFE ANABOLIC SCIENCES